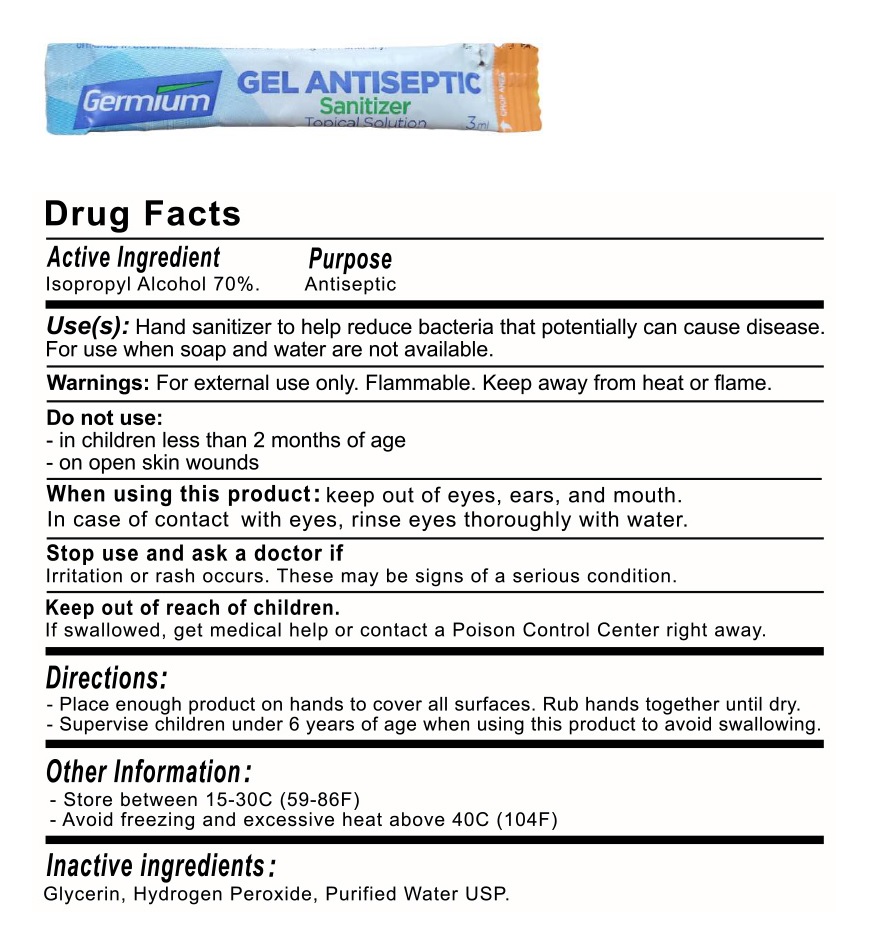 DRUG LABEL: Supply Works LLC
NDC: 80409-001 | Form: GEL
Manufacturer: SUPPLY WORKS LLC
Category: otc | Type: HUMAN OTC DRUG LABEL
Date: 20200915

ACTIVE INGREDIENTS: ISOPROPYL ALCOHOL 70 mL/100 mL
INACTIVE INGREDIENTS: GLYCERIN; HYDROGEN PEROXIDE; WATER

Supply Works LLC Hand Sanitizing

Active Ingredient

Isopropyl Alcohol 70%

Purpose

Antiseptic

Use(s):

Hand sanitizer to help reduce bacteria that potentially can cause disease. For use when soap and water are not available.

Warnings:

For external use only. Flammable. Keep away from heat or flame.

Do not use:

- in children less than 2 months of age

- on open skin wounds

When using this product: keep out of eyes, ears, and mouth. In case of contact with eyes, rinse eyes thoroughly with water.

Stop use and ask a doctor if

Irritation or rash occurs. These may be signs of a serious condition.

Keep out of reach of children.

If swallowed, get medical help or contact a Poison Control Center right away.

Directions:

- Place enough product on hands to cover all surfaces. Rub hands together until dry.

- Supervise children under 6 years of age when using this product to avoid swallowing.

Other Information:

- Store between 15-30C (59-86F)

- Avoid freezing and excessive heat above 40C (104F)

Inactive ingredients:

Glycerin, Hydrogen Peroxide, Purified Water USP.

Germium

GEL ANTISEPTIC Sanitizer

Topical Solution